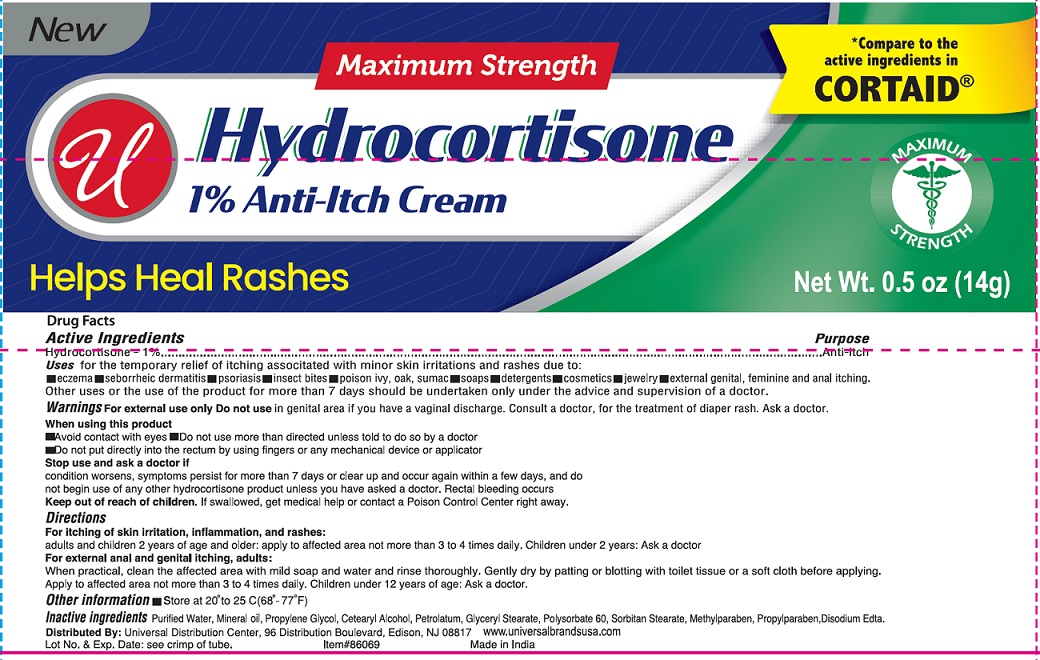 DRUG LABEL: Hydrocortisone Anti-Itch
NDC: 52000-022 | Form: CREAM
Manufacturer: Universal Distribution Center LLC
Category: otc | Type: HUMAN OTC DRUG LABEL
Date: 20251030

ACTIVE INGREDIENTS: HYDROCORTISONE 0.01 g/1 g
INACTIVE INGREDIENTS: WATER; MINERAL OIL; PROPYLENE GLYCOL; CETOSTEARYL ALCOHOL; PETROLATUM; GLYCERYL MONOSTEARATE; POLYSORBATE 60; SORBITAN MONOSTEARATE; METHYLPARABEN; PROPYLPARABEN; EDETATE SODIUM

Hydrocortisone Anti-Itch Cream

Active Ingredient

Hydrocortisone 1%

Purpose

Anti-itch

Uses

for the temporary relief of itching associated with minor skin irritations and rashes due to:

- eczema
- seborrheic dermatitis
- psoriasis
- insect bites
- poison ivy, oak, sumac
- soaps
- detergents
- cosmetics
- jewelry
- external genital, feminine and anal itching

Other uses or the use of the product for more than 7 days should be undertaken only under the advice and supervision of a doctor

Warnings

For external use only

DO NOT USE

Do not usein genital area if you have a vaginal discharge.

Consult a doctor, for the treatment of diaper rash. Ask a doctor.

When using this product

- Avoid contact with eyes
- Do not use more than directed unless told to do so by a doctor
- Do not put directly into the rectum by using fingers or any mechanical device or applicator

Stop use and ask a doctor if

condition worsens, symptoms persist for more than 7 days or clear up and occur again within a few days, and do not begin use of any other hydrocortisone product unless you have asked a doctor. Rectal bleeding occurs.

Keep out of reach of children.

If swallowed, get medical help or contact a Poison Control Center right away.

Directions

For itching of skin irritation, inflammation, and rashes:

adults and children 2 years of age and older: apply to affected area not more than 3 to 4 times daily. Children under 2 years: Ask a doctor

For external anal and genital itching, adults:

When practical, clean the affected area with mild soap and water and rinse thoroughly. Gently dry by patting or blotting with toilet tissue or a soft cloth before applying.
Apply to affected area not more than 3 to 4 times daily. Children under 12 years of age: Ask a doctor.

Other information

- Store at 20ºC to 25º C (68ºF to 77º F)
- Lot No. & Exp. Date: see crimp of tube

Inactive Ingredients

Purified Water, Mineral Oil, Propylene Glycol, Cetearyl Alcohol, Petrolatum, Glyceryl Stearate, Polysorbate 60, Sorbitan Stearate, Methylparaben, Propylparaben, Disodium Edta

PACKAGE LABEL

PRINCIPAL DISPLAY PANEL

HYDROCORTISONE ANTI-ITCH CREAM

NET WT 0.5 OZ. (14 g)